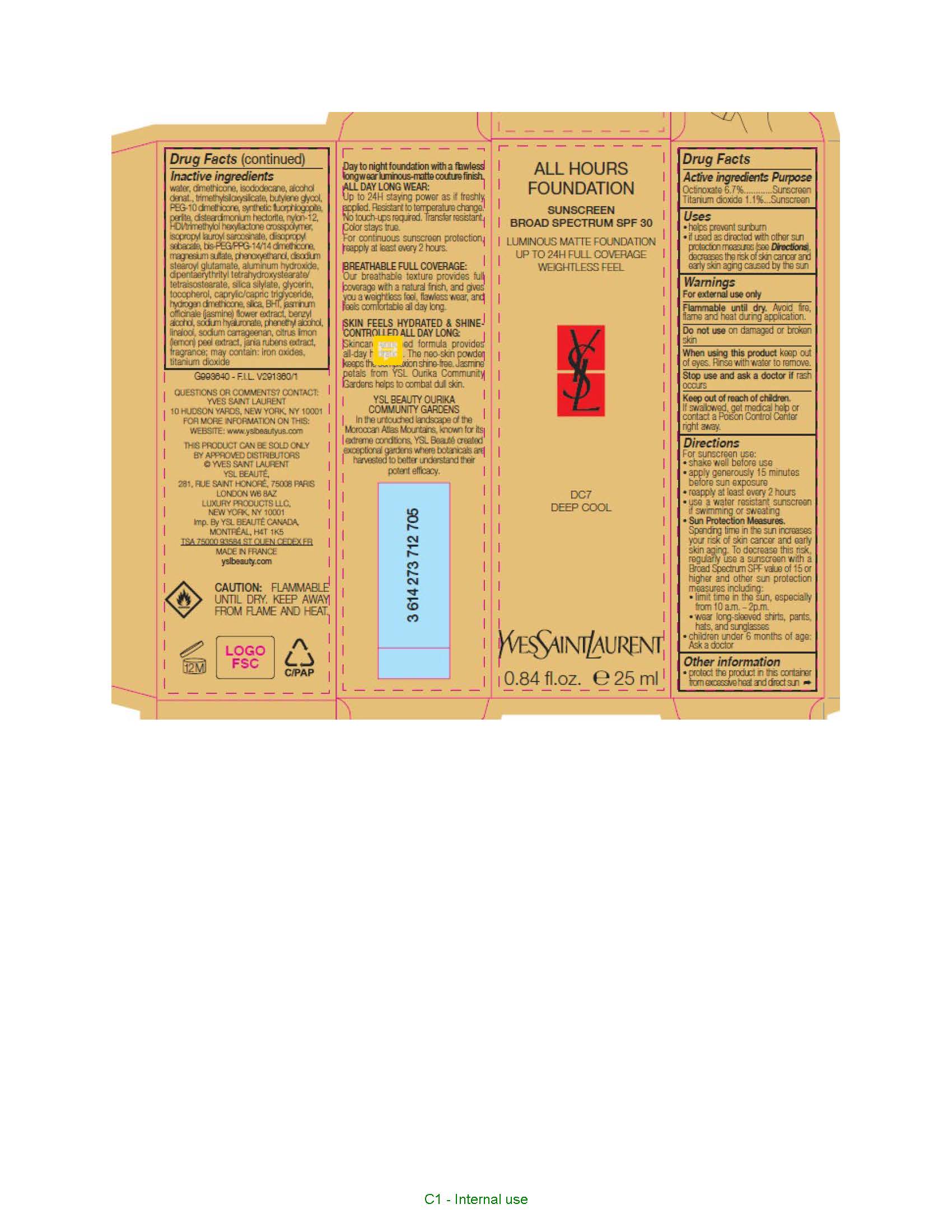 DRUG LABEL: Yves Saint Laurent All Hours Foundation Broad Spectrum SPF 30 Sunscreen Luminous Matte Foundation
NDC: 51150-270 | Form: LOTION
Manufacturer: SICOS ET CIE
Category: otc | Type: HUMAN OTC DRUG LABEL
Date: 20240624

ACTIVE INGREDIENTS: OCTINOXATE 67 mg/1 mL; TITANIUM DIOXIDE 11 mg/1 mL
INACTIVE INGREDIENTS: WATER; DIMETHICONE; ISODODECANE; ALCOHOL; TRIMETHYLSILOXYSILICATE (M/Q 0.6-0.8); BUTYLENE GLYCOL; MAGNESIUM POTASSIUM ALUMINOSILICATE FLUORIDE; PEG-10 DIMETHICONE (600 CST); PERLITE; DISTEARDIMONIUM HECTORITE; NYLON-12; HEXAMETHYLENE DIISOCYANATE/TRIMETHYLOL HEXYLLACTONE CROSSPOLYMER; ISOPROPYL LAUROYL SARCOSINATE; DIISOPROPYL SEBACATE; BIS-PEG/PPG-14/14 DIMETHICONE; MAGNESIUM SULFATE, UNSPECIFIED FORM; PHENOXYETHANOL; DISODIUM STEAROYL GLUTAMATE; DIPENTAERYTHRITYL TETRAHYDROXYSTEARATE/TETRAISOSTEARATE; GLYCERIN; TOCOPHEROL; MEDIUM-CHAIN TRIGLYCERIDES; HYDROGEN DIMETHICONE (13 CST); SILICON DIOXIDE; BUTYLATED HYDROXYTOLUENE; JASMINUM OFFICINALE FLOWER; BENZYL ALCOHOL; HYALURONATE SODIUM; PHENYLETHYL ALCOHOL; LINALOOL, (+/-)-; CARRAGEENAN; LEMON PEEL; FERRIC OXIDE RED

Drug Facts

Active ingredientS

Octinoxate 6.7%

Titanium dioxide 1.1%

Purpose

Sunscreen

Uses

- helps prevent sunburn
- if used as directed with other sun protection measures (see Directions), decreases the risk of skin cancer and early skin aging caused by the sun

Warnings

For external use only

Flammable until dry.

Avoid fire, flame and heat during application.

Do not use

on damaged or broken skin

When using this product

keep out of eyes. Rinse with water to remove.

Stop use and ask a doctor if

rash occurs

Keep out of reach of children.

If swallowed, get medical help or contact a Poison Control Center right away.

Directions

For sunscreen use:

- shake well before use
- apply liberally 15 minutes before sun exposure
- reapply at least every 2 hours
- use a water resistant sunscreen if swimming or sweating
- Sun Protection Measures. Spending time in the sun increases your risk of skin cancer and early skin aging. To decrease this risk regularly use a sunscreen with a Broad Spectrum SPF value of 15 or higher and other sun protection measures including:

- limit time in the sun, especially from 10 a.m. - 2 p.m.

- wear long-sleeved shirts, pants, hats and sunglasses

- children under 6 months of age: Ask a doctor

Other information

- protect the product in this container from excessive heat and direct sun

Inactive ingredients

water, dimethicone, isododecane, alcohol denat., trimethylsiloxysilicate, butylene glycol, PEG-10 dimethicone, synthetic fluorphlogopite, perlite, disteardimonium hectorite, nylon-12, HDI/trimethylol hexyllactone crosspolymer, aluminum hydroxide, isopropyl lauroyl sarcosinate, diisopropyl sebacate, bis-PEG/PPG-14/14 dimethicone,magnesium sulfate, phenoxyethanol, disodium stearoyl glutamate, aluminum hydroxide, dipentaerythrityl tetrahydroxystearate/tetraisostearate, silica silylate, glycerin, tocopherol, caprylic/capric triglyceride, hydrogen dimethicone, silica, BHT, jasminum officinale (jasmine) flower extract, benzyl alcohol, sodium hyaluronate, phenethyl alcohol, linalool, sodium carrageenan, citrus limon (lemon) peel extract, jania rubens extract, fragrance; may contain: iron oxides, titanium dioxide